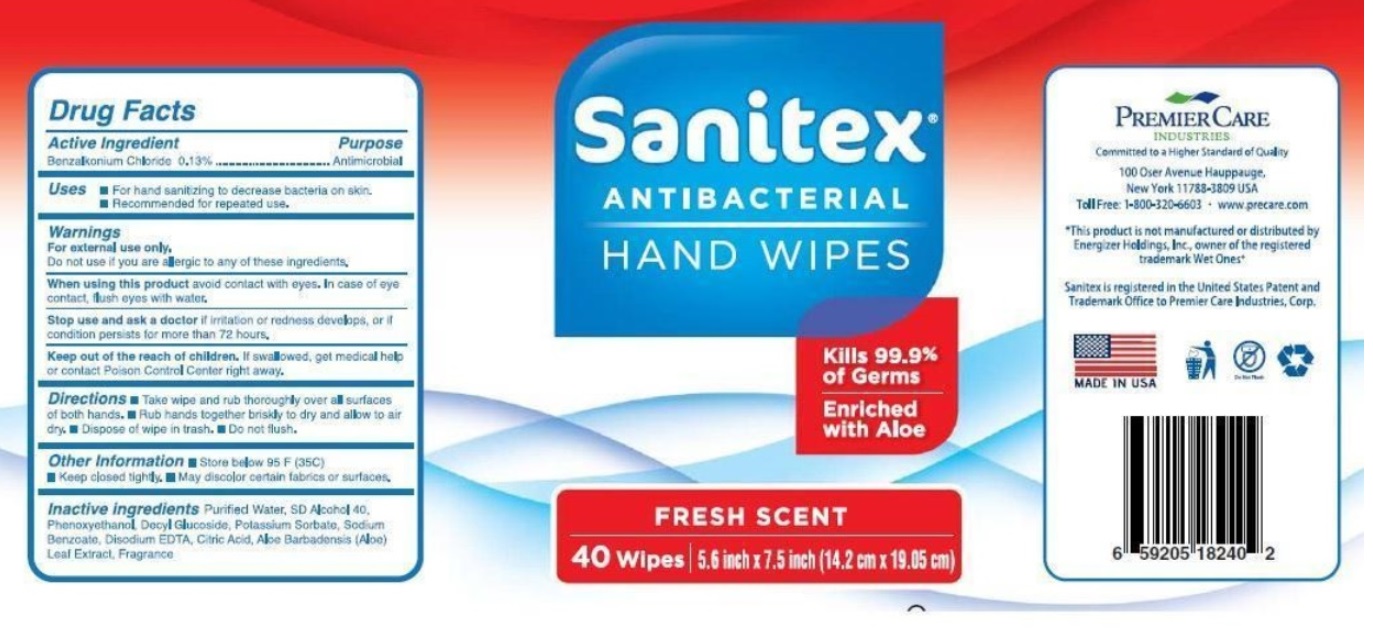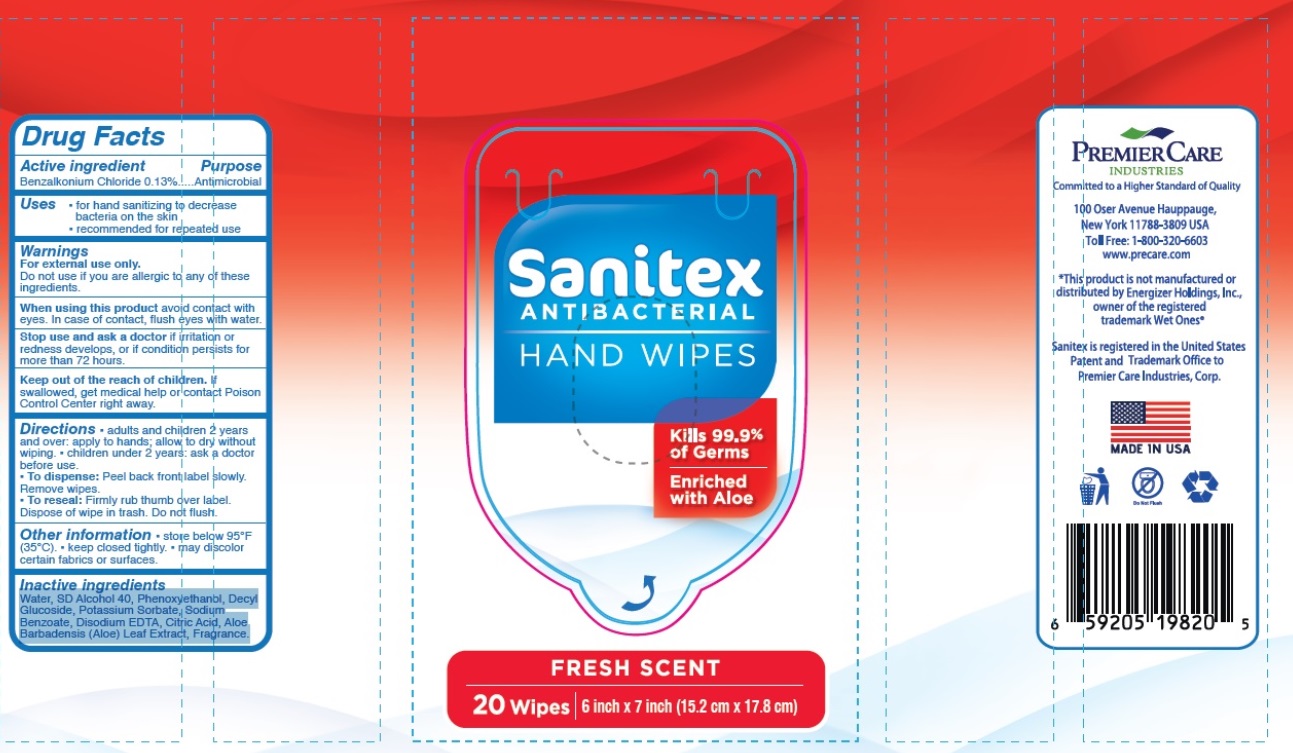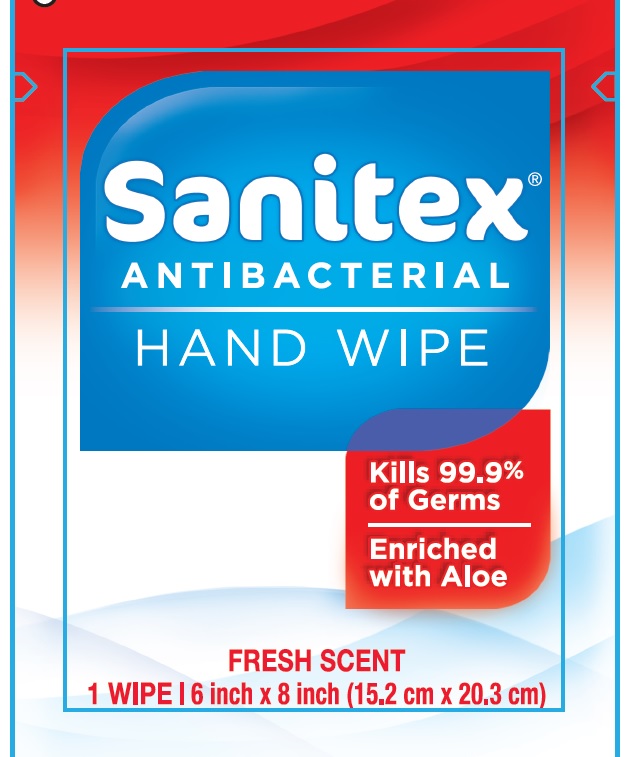 DRUG LABEL: Sanitex Antibacterial Hand Wipes
NDC: 53118-002 | Form: SWAB
Manufacturer: Precare Corp
Category: otc | Type: HUMAN OTC DRUG LABEL
Date: 20251205

ACTIVE INGREDIENTS: BENZALKONIUM CHLORIDE 0.13 g/100 g
INACTIVE INGREDIENTS: ALCOHOL; WATER; PHENOXYETHANOL; DECYL GLUCOSIDE; POTASSIUM SORBATE; SODIUM BENZOATE; EDETATE DISODIUM; CITRIC ACID MONOHYDRATE; ALOE VERA LEAF

Drug Facts

Active Ingredient

Benzalkonium Chloride 0.13%

Purpose

Antimicrobial

Uses

- For hand sanitizing to decrease bacteria on skin.
- Recommended for repeated use.

Warnings

For external use only.

Do not use if

you are allergic to any of these ingredients.

When using this product

avoid contact with eyes. In case of eye contact, flush eyes with water.

Stop use and ask a doctor

if irritation or redness develops, or if condition persists for more than 72 hours.

Keep out of the reach children.

If swallowed, get medical help or contact Poison Control Center right away.

Directions

adults and children 2 years and over:

apply to hands; allow to dry without wiping.

children under 2 years: ask a doctor before use.

- To dispense: Peel back front label slowly. Remove wipes.
- To reseal: Firmly rub thumb over label.

Dispose of wipe in trash. Do not flush.

For single wipe sachet

- Take wipe and rub thoroughly over all surfaces of both hands. Wet hands thoroughly with wipe.
- Rub hands together briskly to dry without wiping.
- Dispose of wipe
- Do not flush

Other Information

- Store below 95 F (35 C)
- Keep closed tightly.
- May discolor certain fabrics or surfaces.

For single sachet

store in a cool dry place

Inactive ingredients

Water, SD Alcohol 40, Phenoxyethanol, Decyl Glucoside, Potassium Sorbate, Sodium Benzoate, Disodium EDTA, Citric Acid, Aloe Barbadensis (Aloe) Leaf Extract, Fragrance

Principal Display Panel

NDC 53118-002-01

Sanitex®

Antibacterial

HAND WIPES

Kills 99.9% of Germs

Enriched with Aloe

FRESH SCENT

40 wipes| 5.6 inch x 7.5 inch (14.2 cm x 19.05 cm)

NDC 53118-002-02

Sanitex®

Antibacterial

HAND WIPES

Kills 99.9% of Germs

Enriched with Aloe

FRESH SCENT

20 wipes| 6 inch x 7 inch (15.2 cm x 17.8 cm)

NDC 53118-002-03

Sanitex®

Antibacterial

HAND WIPE

Kills 99.9% of Germs

Enriched with Aloe

FRESH SCENT

1 Wipe | 6 inch X 8 inch (15.2 cm X 20.3 cm)